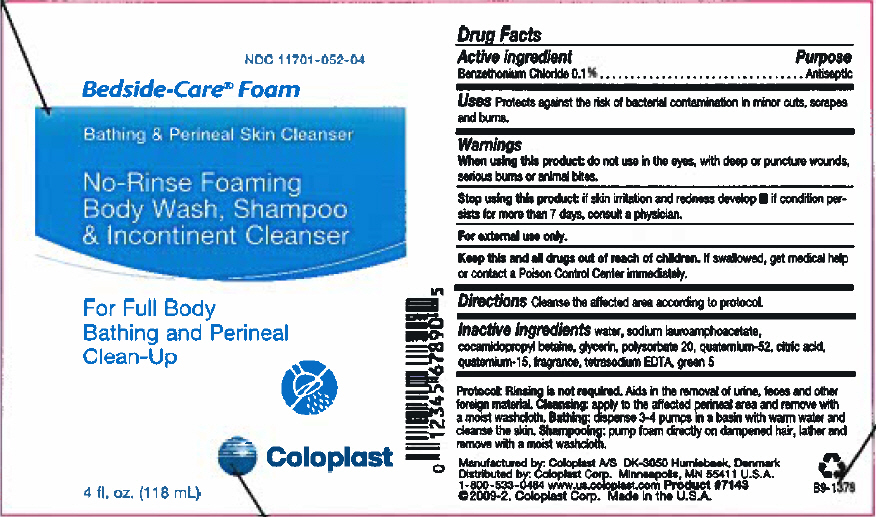 DRUG LABEL: Bedside-Care Foam 
NDC: 11701-052 | Form: SHAMPOO
Manufacturer: Coloplast Manufacturing US, LLC
Category: otc | Type: HUMAN OTC DRUG LABEL
Date: 20180215

ACTIVE INGREDIENTS: BENZETHONIUM CHLORIDE 100 mg/100 mL
INACTIVE INGREDIENTS: D&C GREEN NO. 5; CITRIC ACID MONOHYDRATE; EDETATE SODIUM; QUATERNIUM-15; POLYSORBATE 20; COCAMIDOPROPYL BETAINE; QUATERNIUM-52; GLYCERIN; WATER

Bedside-Care® Foam
Bathing & Perineal Skin Cleanser
No-Rinse Foaming
Body Wash, Shampoo
& Incontinent Cleanser

For Full-Body Bathing And Perineal Clean-Up

Drug Facts

Active ingredient

Benzethonium Chloride 0.1%

Purpose

Antiseptic

INDICATIONS AND USAGE

Uses Protects against the risk of bacterial contamination in minor cuts, scraps and burns.

Warnings

When using this product: do not use in the eyes, with deep or puncture wounds, serious burns, or animal bites.

Stop using this product:

- if skin irritation and redness develop
- if condition persists for more than 7 days, consult a physician.

For external use only.

KEEP OUT OF REACH OF CHILDREN

Keep this and all drugs out of the reach of children. If swallowed, get medical help or contact a Poison Control Center immediately.

DOSAGE AND ADMINISTRATION

Directions Cleanse the affected area according to protocol.

INACTIVE INGREDIENT

Inactive ingredients purified water, sodium lauroamphoacetate, cocamidopropyl betaine, glycerin, polysorbate 20, quaternium-52, citric acid, quaternium-15, fragrance, tetrasodium EDTA, green 5

Protocol: Rinsing is not required. Aids in the removal of urine, feces and other foreign material. Cleansing: apply to the affected perineal area and remove with a moist washcloth. Bathing: dispense 3-4 pumps in a basin with warm water and cleanse the skin. Shampooing: pump foam directly on dampened hair, lather and remove with a moist washcloth.

Manufactured by: Coloplast A/S DK-3050 Humlebaek, Denmark
Distributed by: Coloplast Corp., Minneapolis, MN 55411 U.S.A.
1-800-533-0464 www.us.coloplast.com ©2007, Coloplast Corp.
Product #7145 Made in the U.S.A.

G7-1276

PRINCIPAL DISPLAY PANEL - 118 mL Bottle Label

NDC 11701-052-04

Bedside-Care® Foam

Bathing & Perineal Skin Cleanser

No-Rinse Foaming
Body Wash, Shampoo
& Incontinent Cleanser

For Full Body
Bathing and Perineal
Clean-Up

Coloplast

4 fl. oz. (118 mL)